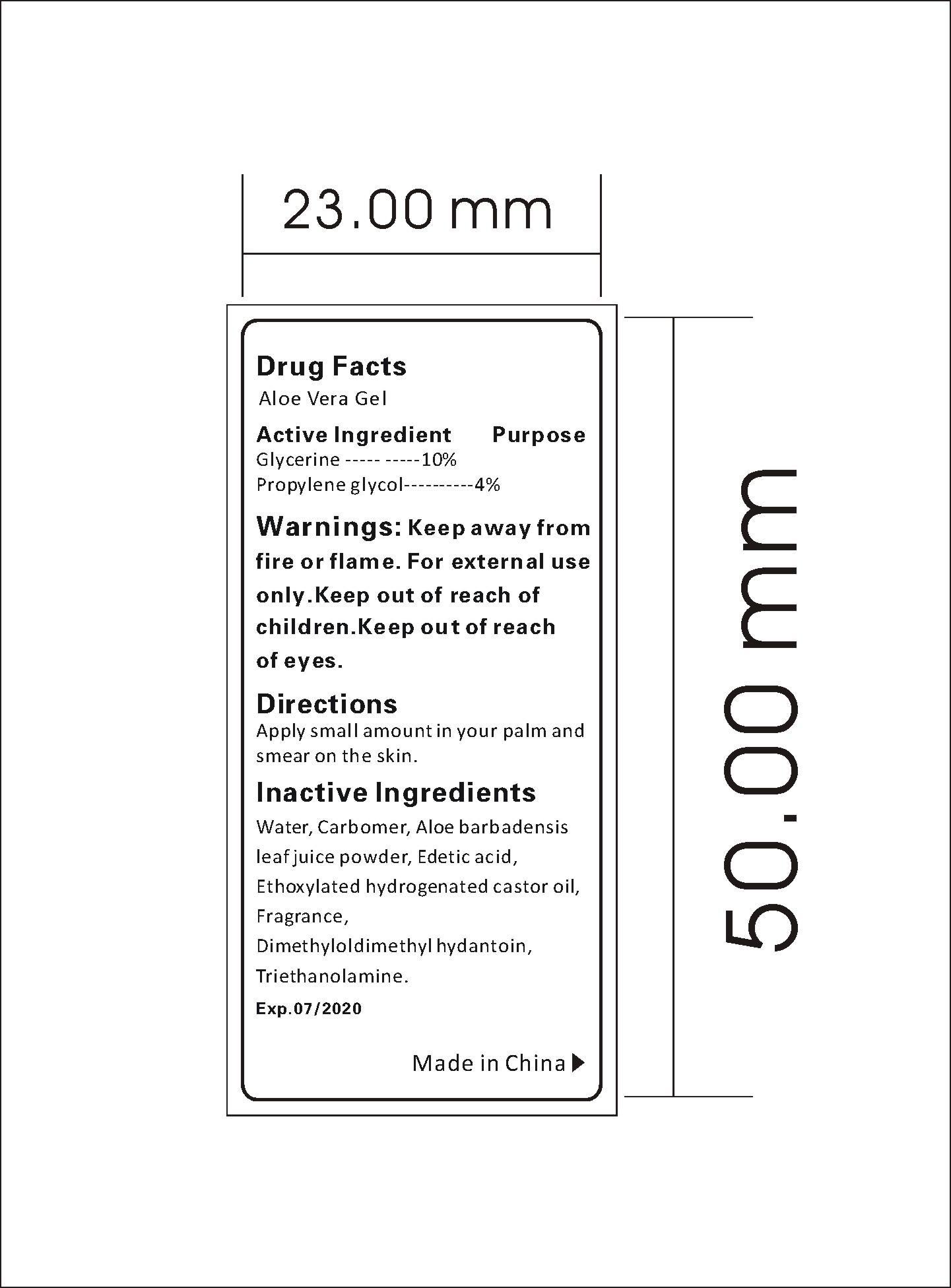 DRUG LABEL: Aloe Vera Gel
NDC: 47993-220 | Form: GEL
Manufacturer: NINGBO JIANGBEI OCEAN STAR TRADING CO.,LTD
Category: otc | Type: HUMAN OTC DRUG LABEL
Date: 20201103

ACTIVE INGREDIENTS: GLYCERIN 10 g/100 g; PROPYLENE GLYCOL 4 g/100 g
INACTIVE INGREDIENTS: WATER 82 g/100 g; CARBOMER 940 0.8 g/100 g; ALOE 0.2 g/100 g; EDETIC ACID 0.1 g/100 g; HYDROGENATED COCONUT OIL 1 g/100 g; AROMADENDRIN 0.5 g/100 g; DMDM HYDANTOIN 0.5 g/100 g; TRIETHANOLAMINE BENZOATE 0.9 g/100 g

47993-220

Active ingredients--------------purpose

Glycerine..........10%

Propylene Glycol..........4%

Uses:
Keep skin moist. Recommended for repeated use.

Warnings:

Keep away from fire or flame.For external use only.Keep out of reach of children.Keep out of reach of eyes.

Directions:

Apply small amount in your palm and smear on the skin.

Other Information

Do not store above 110F(43C) May discolor certain fabric or surfaces. Harmful to wood finishes and plastics.

KEEP OUT OF REACH OF CHILDREN

Children under 6 years of age should be super vised when using this product.

Inactive Ingredients:

Water,Carbomer,Aloe barbadensis leaf juice power,Edetic acid,Ethoxylated hydrogenated castor oil,Fragrance,Dimethyloldimethy hydantoin,Triethanolamine.